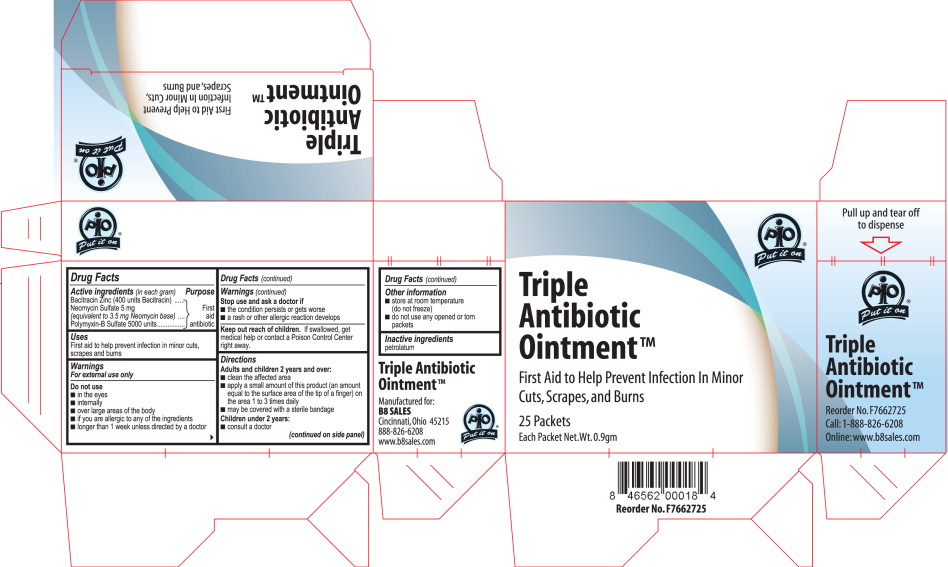 DRUG LABEL: Triple Antibiotic
NDC: 50607-5600 | Form: OINTMENT
Manufacturer: B8 Sales, Inc.
Category: otc | Type: HUMAN OTC DRUG LABEL
Date: 20100402

ACTIVE INGREDIENTS: Bacitracin Zinc 400 1/1 g; Neomycin Sulfate 5 mg/1 g; Polymyxin B Sulfate 5000 1/1 g
INACTIVE INGREDIENTS: petrolatum

PIO Put it on®

Triple Antibiotic Ointment™

First Aid to Help Prevent Infection In Minor Cuts, Scrapes, and Burns

25 Packets

Each Packet Net.Wt.0.9gm

Active ingredients (in each gram)

Bacitradn Zinc (400 units Bacitracin)

Neomycin Sulfate 5 mg

(equivalent to 3.5 mg Neomycin base)

Polymyxin-B Sulfate 5000 units

Purpose

First aid antibiotic

Uses

First aid to help prevent infection in minor cuts, scrapes and burns

Warnings

For external use only

Do not use

- in the eyes
- internally
- over large areas of the body
- if you are allergic to any of the ingredients
- longer than 1 week unless directed by a doctor

Stop use and ask a doctor If

- the condition persists or gets worse
- a rash or other allergic reaction develops

Keep out reach of children. If swallowed, get

medical help or contact a Poison Control Center right away.

Directions

Adults and children 2 years and over:

- clean the affected area
- apply a small amount of this product (an amount equal to the surface area of the tip of a finger) on the area 1 to 3 times dally
- may be covered with a sterile bandage

Children under 2 years:

- consult a doctor

Other information

- store at room temperature (do not freeze)
- do not use any opened or torn packets

Inactive ingredients

petrolatum

Triple Antibiotic Ointment™

Manufactured for:

B8 SALES

Cincinnati,0hio 4521S

888-826-6208

www.b8sales.com

PIO Put it on®

Principal Display Panel

Triple Antibiotic Ointment – Carton Label

PIO Put it on®

Triple Antibiotic Ointment™

First Aid to Help Prevent Infection In Minor Cuts, Scrapes, and Burns

25 Packets

Each Packet Net.Wt.0.9gm